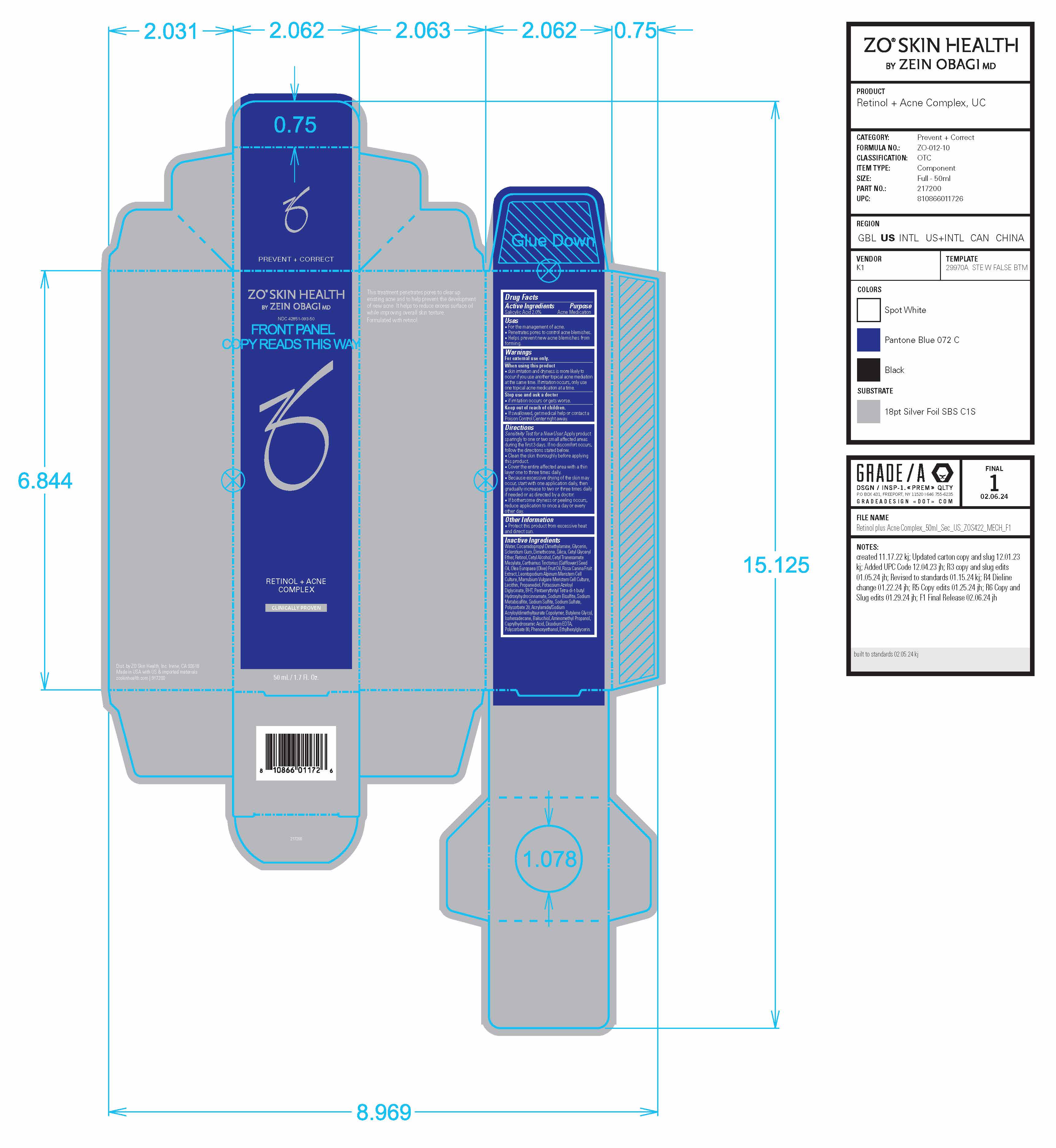 DRUG LABEL: ZO Skin Health Retinol Plus Acne Complex
NDC: 42851-093 | Form: LOTION
Manufacturer: ZO Skin Health, Inc.
Category: otc | Type: HUMAN OTC DRUG LABEL
Date: 20241001

ACTIVE INGREDIENTS: SALICYLIC ACID 1 mg/50 mL
INACTIVE INGREDIENTS: AMINOMETHYLPROPANOL; BAKUCHIOL; COCAMIDOPROPYL DIMETHYLAMINE; RETINOL; OLIVE OIL; POTASSIUM AZELOYL DIGLYCINATE; SODIUM BISULFITE; ISOHEXADECANE; BUTYLATED HYDROXYTOLUENE; PENTAERYTHRITOL TETRAKIS(3-(3,5-DI-TERT-BUTYL-4-HYDROXYPHENYL)PROPIONATE); ETHYLHEXYLGLYCERIN; DIMETHICONE, UNSPECIFIED; LECITHIN, SUNFLOWER; CAPRYLHYDROXAMIC ACID; SODIUM SULFATE; CETYL GLYCERYL ETHER; PROPANEDIOL; ROSA CANINA FRUIT; WATER; SILICON DIOXIDE; BETASIZOFIRAN; SODIUM METABISULFITE; POLYSORBATE 20; BUTYLENE GLYCOL; EDETATE DISODIUM; PHENOXYETHANOL; GLYCERIN; POLYSORBATE 80; SODIUM SULFITE; SAFFLOWER SEED; CETYL ALCOHOL

ZO® Skin Health Retinol + Acne Complex (Formula No. ZO-012-10)
National Drug Code 42851-093-50

Drug Facts

Active Ingredients

Active Ingredients | Purpose
Salicylic Acid 2.0% | Acne Medication

Uses

- For the management of acne.
- Penetrates pores to control acne blemishes.
- Helps prevent new acne blemishes from forming.

Warnings

OTHER SAFETY INFORMATION

For external use only.

When using this product

- skin irritation and dryness is more likely to occur if you use another topical acne mediation at the same time. If irritation occurs, only use one topical acne medication at a time.

Stop use and ask a doctor

- if irritation occurs or gets worse.

Keep out of reach of children.

- If swallowed, get medical help or contact a Poison Control Center right away.

Directions

Sensitivity Test for a New User. Apply product sparingly to one or two small affected areas during the first 3 days. If no discomfort occurs, follow the directions stated below.

- Clean the skin thoroughly before applying this product.
- Cover the entire affected area with a thin layer one to three times daily.
- Because excessive drying of the skin may occur, start with one application daily, then gradually increase to two or three times daily if needed or as directed by a doctor.
- If bothersome dryness or peeling occurs, reduce application to once a day or every other day.

Other Information

- Protect this product from excessive heat and direct sun.

Inactive Ingredients

Water, Cocamidopropyl Dimethylamine, Glycerin,
Sclerotium Gum, Dimethicone, Silica, Cetyl Glyceryl
Ether, Retinol, Cetyl Alcohol, Cetyl Tranexamate
Mesylate, Carthamus Tinctorius (Safflower) Seed
Oil, Olea Europaea (Olive) Fruit Oil, Rosa Canina Fruit
Extract, Leontopodium Alpinum Meristem Cell
Culture, Marrubium Vulgare Meristem Cell Culture,
Lecithin, Propanediol, Potassium Azeloyl
Diglycinate, BHT, Pentaerythrityl Tetra-di-t-butyl
Hydroxyhydrocinnamate, Sodium Bisulfite, Sodium
Metabisulfite, Sodium Sulfite, Sodium Sulfate,
Polysorbate 20, Acrylamide/Sodium
Acryloyldimethyltaurate Copolymer, Butylene Glycol,
Isohexadecane, Bakuchiol, Aminomethyl Propanol,
Caprylhydroxamic Acid, Disodium EDTA,
Polysorbate 80, Phenoxyethanol, Ethylhexylglycerin.

Principal Display Panel

ZO® SKIN HEALTH
BY ZEIN OBAGI, MD

NDC 42851-093-50

RETINOL + ACNE COMPLEX
50 mL / 1.7 Fl. Oz.

Dist. by ZO Skin Health, Inc. Irvine, CA 92618
Made in USA with US & imported materials
zoskinhealth.com | 917200